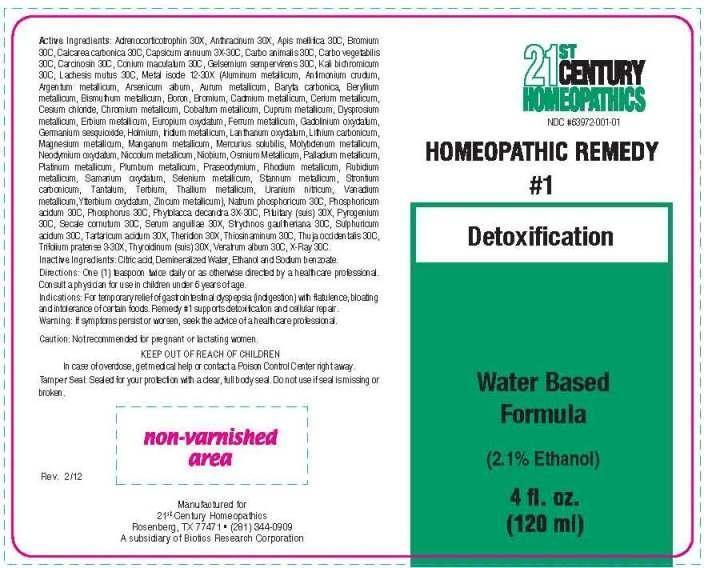 DRUG LABEL: 1 Detoxification
NDC: 63972-001 | Form: LIQUID
Manufacturer: 21st Century Homeopathics
Category: homeopathic | Type: HUMAN OTC DRUG LABEL
Date: 20150812

ACTIVE INGREDIENTS: CAPSICUM 3 [hp_X]/1 mL; PHYTOLACCA AMERICANA ROOT 3 [hp_X]/1 mL; TRIFOLIUM PRATENSE FLOWER 3 [hp_X]/1 mL; ALUMINUM 12 [hp_X]/1 mL; ANTIMONY TRISULFIDE 12 [hp_X]/1 mL; SILVER 12 [hp_X]/1 mL; ARSENIC TRIOXIDE 12 [hp_X]/1 mL; GOLD 12 [hp_X]/1 mL; BARIUM CARBONATE 12 [hp_X]/1 mL; BERYLLIUM 12 [hp_X]/1 mL; BISMUTH 12 [hp_X]/1 mL; BORON 12 [hp_X]/1 mL; CADMIUM 12 [hp_X]/1 mL; CERIUM 12 [hp_X]/1 mL; CESIUM CHLORIDE 12 [hp_X]/1 mL; CHROMIUM 12 [hp_X]/1 mL; COBALT 12 [hp_X]/1 mL; COPPER 12 [hp_X]/1 mL; DYSPROSIUM 12 [hp_X]/1 mL; ERBIUM 12 [hp_X]/1 mL; EUROPIUM OXIDE 12 [hp_X]/1 mL; IRON 12 [hp_X]/1 mL; GADOLINIUM OXIDE 12 [hp_X]/1 mL; GERMANIUM SESQUIOXIDE 12 [hp_X]/1 mL; HOLMIUM 12 [hp_X]/1 mL; INDIUM 12 [hp_X]/1 mL; LANTHANUM OXIDE 12 [hp_X]/1 mL; LITHIUM CARBONATE 12 [hp_X]/1 mL; MAGNESIUM 12 [hp_X]/1 mL; MANGANESE 12 [hp_X]/1 mL; MERCURIUS SOLUBILIS 12 [hp_X]/1 mL; MOLYBDENUM 12 [hp_X]/1 mL; NEODYMIUM OXIDE 12 [hp_X]/1 mL; NICKEL 12 [hp_X]/1 mL; NIOBIUM 12 [hp_X]/1 mL; OSMIUM 12 [hp_X]/1 mL; PALLADIUM 12 [hp_X]/1 mL; PLATINUM 12 [hp_X]/1 mL; LEAD 12 [hp_X]/1 mL; PRASEODYMIUM 12 [hp_X]/1 mL; RHODIUM 12 [hp_X]/1 mL; RUBIDIUM 12 [hp_X]/1 mL; SAMARIUM OXIDE 12 [hp_X]/1 mL; SELENIUM 12 [hp_X]/1 mL; TIN 12 [hp_X]/1 mL; STRONTIUM CARBONATE 12 [hp_X]/1 mL; TANTALUM 12 [hp_X]/1 mL; TERBIUM 12 [hp_X]/1 mL; THALLIUM 12 [hp_X]/1 mL; URANYL NITRATE HEXAHYDRATE 12 [hp_X]/1 mL; VANADIUM 12 [hp_X]/1 mL; YTTERBIUM OXIDE 12 [hp_X]/1 mL; ZINC 12 [hp_X]/1 mL; CORTICOTROPIN 30 [hp_X]/1 mL; BACILLUS ANTHRACIS IMMUNOSERUM RABBIT 30 [hp_X]/1 mL; SUS SCROFA PITUITARY GLAND 30 [hp_X]/1 mL; ANGUILLA ROSTRATA BLOOD SERUM 30 [hp_X]/1 mL; TARTARIC ACID 30 [hp_X]/1 mL; THERIDION CURASSAVICUM 30 [hp_X]/1 mL; SUS SCROFA THYROID 30 [hp_X]/1 mL; APIS MELLIFERA 30 [hp_C]/1 mL; BROMINE 30 [hp_C]/1 mL; OYSTER SHELL CALCIUM CARBONATE, CRUDE 30 [hp_C]/1 mL; CARBO ANIMALIS 30 [hp_C]/1 mL; ACTIVATED CHARCOAL 30 [hp_C]/1 mL; HUMAN BREAST TUMOR CELL 30 [hp_C]/1 mL; CONIUM MACULATUM FLOWERING TOP 30 [hp_C]/1 mL; GELSEMIUM SEMPERVIRENS ROOT 30 [hp_C]/1 mL; POTASSIUM DICHROMATE 30 [hp_C]/1 mL; LACHESIS MUTA VENOM 30 [hp_C]/1 mL; SODIUM PHOSPHATE, DIBASIC, HEPTAHYDRATE 30 [hp_C]/1 mL; PHOSPHORIC ACID 30 [hp_C]/1 mL; PHOSPHORUS 30 [hp_C]/1 mL; RANCID BEEF 30 [hp_C]/1 mL; CLAVICEPS PURPUREA SCLEROTIUM 30 [hp_C]/1 mL; STRYCHNOS WALLICHIANA BARK 30 [hp_C]/1 mL; SULFURIC ACID 30 [hp_C]/1 mL; ALLYLTHIOUREA 30 [hp_C]/1 mL; THUJA OCCIDENTALIS LEAFY TWIG 30 [hp_C]/1 mL; VERATRUM ALBUM ROOT 30 [hp_C]/1 mL; ALCOHOL, X-RAY EXPOSED (1000 RAD) 30 [hp_C]/1 mL
INACTIVE INGREDIENTS: CITRIC ACID MONOHYDRATE; SODIUM BENZOATE; WATER; ALCOHOL

DRUG FACTS:

ACTIVE INGREDIENTS:

CAPSICUM ANNUUM 3X, 30C, PHYTOLACCA DECANDRA 3X, 30C, TRIFOLIUM PRATENSE 3X, 30X, ALUMINUM METALLICUM 12X, 30X, ANTIMONIUM CRUDUM 12X, 30X, ARGENTUM METALLICUM 12X, 30X, ARSENICUM ALBUM 12X, 30X, AURUM METALLICUM 12X, 30X, BARYTA CARBONICA 12X, 30X, BERYLLIUM METALLICUM 12X, 30X, BISMUTHUM METALLICUM 12X, 30X, BORON 12X, 30X, BROMIUM 12X, 30X, CADMIUM METALLICUM 12X, 30X, CERIUM METALLICUM 12X, 30X, CESIUM CHLORIDE 12X, 30X, CHROMIUM METALLICUM 12X, 30X, COBALTUM METALLICUM 12X, 30X, CUPRUM METALLICUM 12X, 30X, DYSPROSIUM METALLICUM 12X, 30X, ERBIUM METALLICUM 12X, 30X, EUROPIUM OXYDATUM 12X, 30X, FERRUM METALLICUM 12X, 30X, GADOLINIUM OXYDATUM 12X, 30X, GERMANIUM SESQUIOXIDE 12X, 30X, HOLMIUM 12X, 30X, INDIUM METALLICUM 12X, 30X, LANTHANUM OXYDATUM 12X, 30X, LITHIUM CARBONICUM 12X, 30X, MAGNESIUM METALLICUM 12X, 30X, MANGANUM METALLICUM 12X, 30X, MERCURIUS SOLUBILIS 12X, 30X, MOLYBDENUM METALLICUM 12X, 30X, NEODYMIUM OXYDATUM 12X, 30X, NICCOLUM METALLICUM 12X, 30X, NIOBIUM 12X, 30X, OSMIUM METALLICUM 12X, 30X, PALLADIUM METALLICUM 12X, 30X, PLATINUM METALLICUM 12X, 30X, PLUMBUM METALLICUM 12X, 30X, PRASEODYMIUM 12X, 30X, RHODIUM METALLICUM 12X, 30X, RUBIDIUM METALLICUM 12X, 30X, SAMARIUM OXYDATUM 12X, 30X, SELENIUM METALLICUM 12X, 30X, STANNUM METALLICUM 12X, 30X, STRONTIUM CARBONICUM 12X, 30X, TANTALUM 12X, 30X, TERBIUM 12X, 30X, THALLIUM METALLICUM 12X, 30X, URANIUM NITRICUM 12X, 30X, VANADIUM METALLICUM 12X, 30X, YTTERBIUM OXYDATUM 12X, 30X, ZINCUM METALLICUM 12X, 30X, ADRENOCORTICOTROPHIN 30X, ANTHRACINUM 30X, PITUITARIA GLANDULA (SUIS) 30X, SERUM ANGUILLAE 30X, TARTARICUM ACIDUM 30X, THERIDION 30X, THYROIDINUM (SUIS) 30X, APIS MELLIFICA 30C, BROMIUM 30C, CALCAREA CARBONICA 30C, CARBO ANIMALIS 30C, CARBO VEGETABILIS 30C, CARCINOSIN 30C, CONIUM MACULATUM 30C, GELSEMIUM SEMPERVIRENS 30C, KALI BICHROMICUM 30C, LACHESIS MUTUS 30C, NATRUM PHOSPHORICUM 30C, PHOSPHORICUM ACIDUM 30C, PHOSPHORUS 30C, PYROGENIUM 30C, SECALE CORNUTUM 30C, HOANG-NAN 30C, SULPHURICUM ACIDUM 30C, THIOSINAMINUM 30C, THUJA OCCIDENTALIS 30C, VERATRUM ALBUM 30C, X-RAY 30C.

INDICATIONS:

For temporary relief of gastrointestinal dyspepsia (indigestion) with flatulence, bloating and intolerance of certain foods. Remedy #1 supports detoxification and cellular repair.

WARNINGS:

If symptoms persist or worsen, seek the advice of a healthcare professional.

Caution: Not recommended for pregnant or lactating women.

KEEP OUT OF REACH OF CHILDREN

In case of overdose, get medical help or contact a Poison Control Center right away.

Tamper Seal: Sealed for your protection with a clear, full body seal. Do not use if seal is missing or broken.

KEEP OUT OF REACH OF CHILDREN:

In case of overdose, get medical help or contact a Poison Control Center right away.

DIRECTIONS:

One (1) teaspoon twice daily or as otherwise directed by a healthcare professional.

Consult a physician for use in children under 6 years of age.

INDICATIONS:

For temporary relief of gastrointestinal dyspepsia (indigestion) with flatulence, bloating and intolerance of certain foods. Remedy #1 supports detoxification and cellular repair.

INACTIVE INGREDIENTS:

Citric Acid, Demineralized Water, Ethanol 2.1%, Sodium Benzoate.

QUESTIONS:

Manufactured for

21st Century Homeopathics

Rosenberg, TX 77471 (281) 344-0909

A subsidiary of Biotics Research Corporation

PACKAGE LABEL DISPLAY:

21ST CENTURY

HOMEOPATHICS

NDC #63972-001-01

HOMEOPATHIC REMEDY

#1

Detoxification

Water Based

Formula

(2.1% Ethanol)

4 fl. oz.

(120 ml)